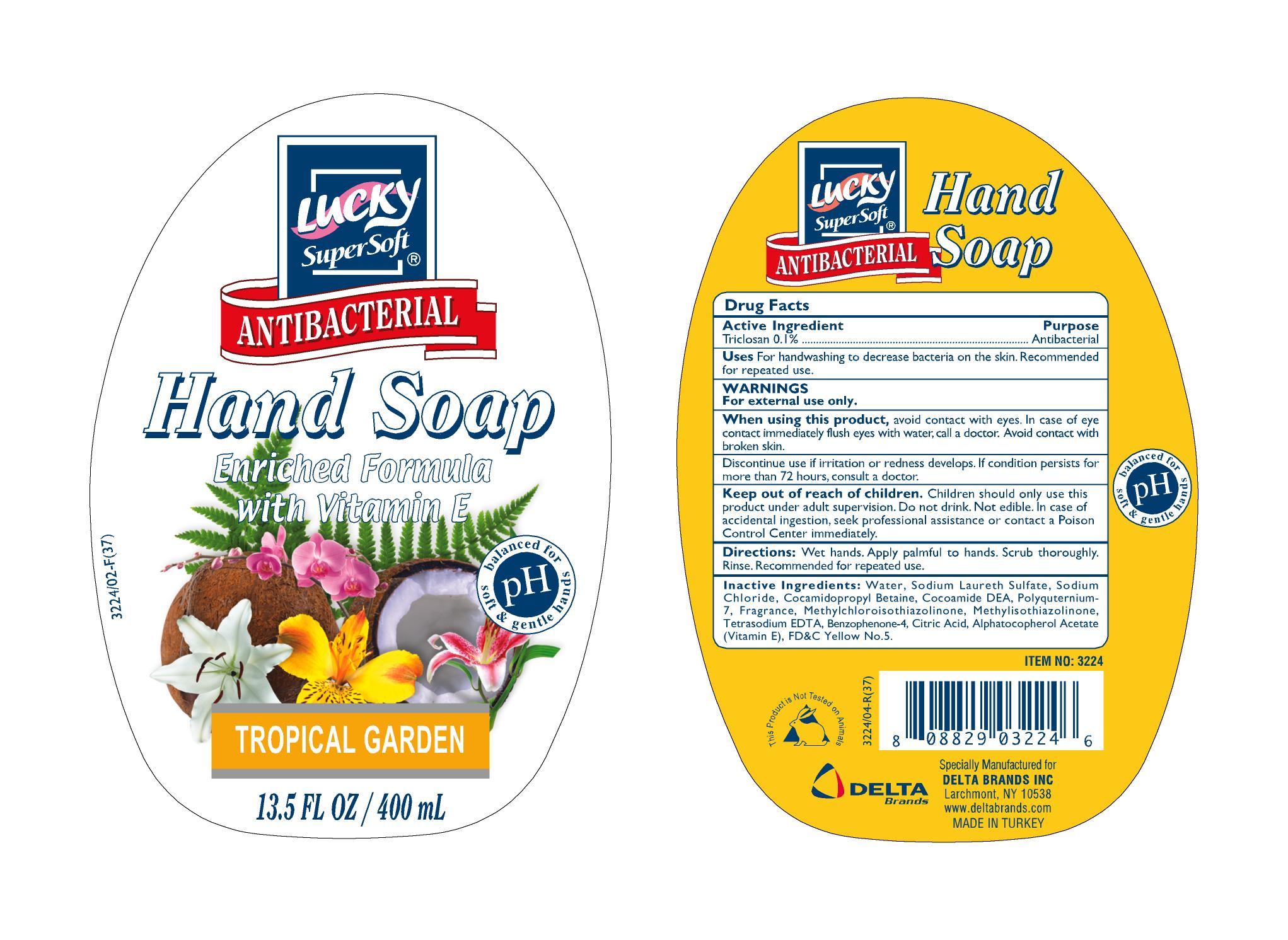 DRUG LABEL: Lucky Antibacterial Hand Soap
NDC: 20276-164 | Form: LIQUID
Manufacturer: Delta Brands Inc
Category: otc | Type: HUMAN OTC DRUG LABEL
Date: 20100818

ACTIVE INGREDIENTS: TRICLOSAN 0.1 mL/100 mL
INACTIVE INGREDIENTS: WATER; SODIUM LAURETH SULFATE; SODIUM CHLORIDE; COCAMIDOPROPYL BETAINE; COCO DIETHANOLAMIDE; POLYQUATERNIUM-7 (70/30 ACRYLAMIDE/DADMAC; 900 KD); METHYLCHLOROISOTHIAZOLINONE; METHYLISOTHIAZOLINONE; EDETATE SODIUM; BENZOPHENONE; CITRIC ACID MONOHYDRATE; ALPHA-TOCOPHEROL ACETATE; FD&C YELLOW NO. 5

Drug Facts

Active Ingredient

Triclosan 0.1%

Purpose

Antibacterial

Uses

For handwashing to decrease bacteria on the skin. Recommended for repeated use.

Warnings

For external use only

When using this product

avoid contact with eyes. In case of eye contact immediately flush eyes with water, call a doctor. Avoid contact with broken skin.
Discontinue use if irritation or redness develops. If condition persists for more than 72 hours, consult a doctor.

Keep out of reach of children

Children can only use this product with adult supervision. Do not drink. Not edible. In case of accidental ingestion seek professional assistance or contact Poison Control Center immediately.

Directions

Wet hands. Apply palmful to hands. Scrub thoroughly. Rinse. Recommended for repeated use

INACTIVE INGREDIENT

Water, Sodium Laureth Sulfate, Sodium Chloride, Cocamidopropyl Betaine, Cocamide DEA, Polyquaternium-7, Fragrance, Methylchloroisothiazolinone, Methylisothiazolinone, Tetrasodium EDTA, Benzophenone-4, Citric Acid, Alphatocopherol Acetate (Vitamin E), FDC Yellow No. 5

Package Label